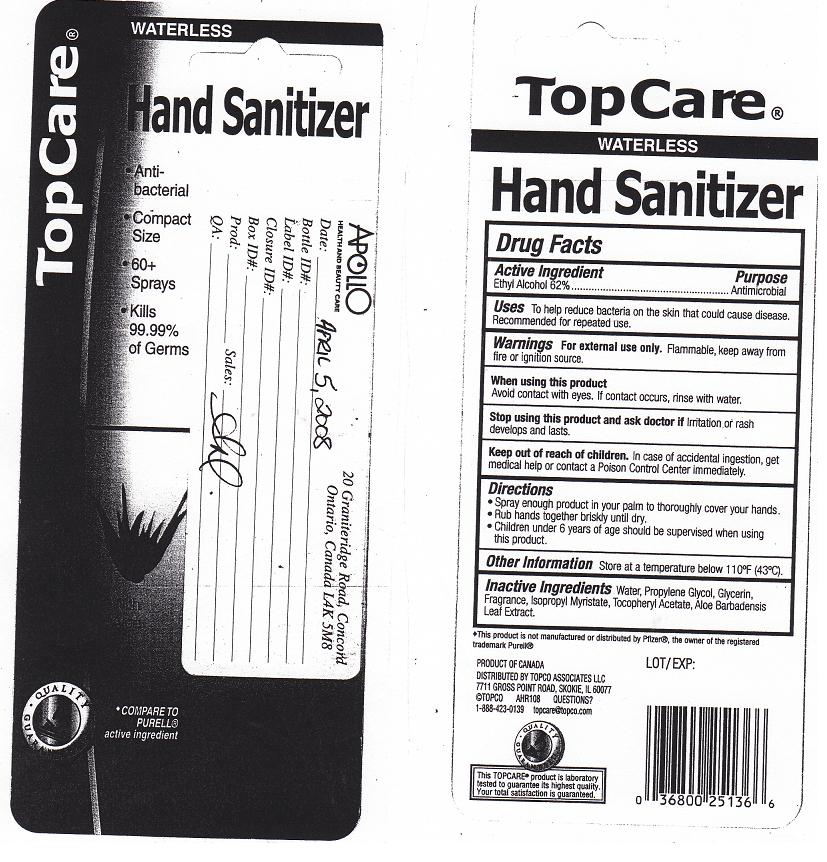 DRUG LABEL: TOPCARE
NDC: 36800-235 | Form: GEL
Manufacturer: TOPCO ASSOCIATES LLC
Category: otc | Type: HUMAN OTC DRUG LABEL
Date: 20111118

ACTIVE INGREDIENTS: ALCOHOL 62 mL/100 mL
INACTIVE INGREDIENTS: WATER; PROPYLENE GLYCOL; GLYCERIN; ISOPROPYL MYRISTATE; TOCOPHEROL; ALOE VERA LEAF

Drug Facts

Active Ingredient

Ethyl Alcohol 62%

Purpose

Antimicrobial

Uses

To help reduce bacteria on the skin that could cause disease. Recommended for repeated use.

Warnings

For external use only. Flammable, keep away from fire or ignition source.

When using this product

Avoid contact with eyes. If contact occurs, rinse with water.

Stop using this product and ask doctor if

Irritation or rash develops and lasts.

Keep out of reach of children.

In case of accidental ingestion, get medical help or contact Poison Control Center immediately.

Directions

Spray enough product in your palm to thoroughly cover your hands. Rub hands together briskly until dry. Children under 6 years of age should be supervised when using this product.

Other information

Store below 110 F (43 C)

Inactive ingredients

Water, Propylene Glycol, Glycerin, Fragrance, Isopropyl Myristate, Tocopheryl acetate, Aloe Barbadensis Leaf Extract.